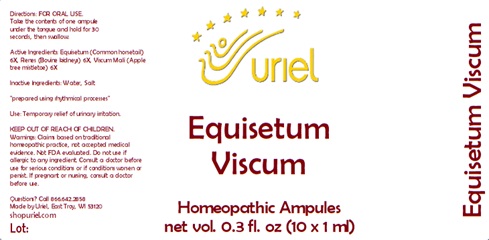 DRUG LABEL: Equisetum Viscum
NDC: 48951-4042 | Form: LIQUID
Manufacturer: Uriel Pharmacy Inc.
Category: homeopathic | Type: HUMAN OTC DRUG LABEL
Date: 20240409

ACTIVE INGREDIENTS: EQUISETUM ARVENSE TOP 6 [hp_X]/1 mL; PORK KIDNEY 6 [hp_X]/1 mL; VISCUM ALBUM FRUITING TOP 6 [hp_X]/1 mL
INACTIVE INGREDIENTS: WATER; SODIUM CHLORIDE

Equisetum Viscum

INDICATIONS AND USAGE

Directions: FOR ORAL USE.

DOSAGE AND ADMINISTRATION

Take the contents of one ampule under the tongue and hold for 30 seconds, then swallow.

ACTIVE INGREDIENT

Active Ingredients: Equisetum (Common horsetail) 6X, Renes (Bovine kidneys) 6X, Viscum Mali (Apple tree mistletoe) 6X

Inactive Ingredients: Water, Salt

prepared using rhythmical processes

PURPOSE

Use: Temporary relief of urinary irritation.

KEEP OUT OF REACH OF CHILDREN.

WARNINGS

Warnings: Claims based on traditional homeopathic practice, not accepted medical evidence. Not FDA evaluated. Do not use if allergic to any ingredient. Consult a doctor before use for serious conditions or if conditions worsen or persist. If pregnant or nursing, consult a doctor before use.

QUESTIONS

Questions? Call 866.642.2858 Made by Uriel, East Troy, WI 53120 shopuriel.com Lot: